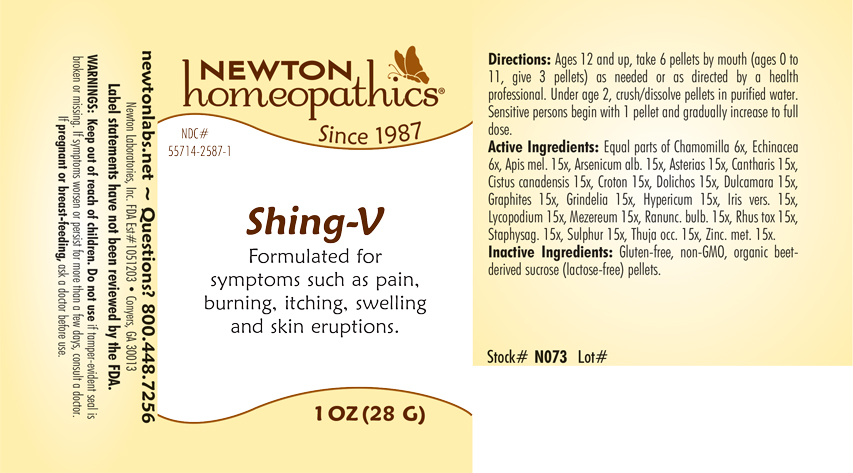 DRUG LABEL: Shing-V
NDC: 55714-2587 | Form: PELLET
Manufacturer: Newton Laboratories, Inc.
Category: homeopathic | Type: HUMAN OTC DRUG LABEL
Date: 20240321

ACTIVE INGREDIENTS: MATRICARIA CHAMOMILLA 6 [hp_X]/1 g; ASTERIAS RUBENS 15 [hp_X]/1 g; LYTTA VESICATORIA 15 [hp_X]/1 g; HELIANTHEMUM CANADENSE 15 [hp_X]/1 g; CROTON TIGLIUM SEED 15 [hp_X]/1 g; MUCUNA PRURIENS FRUIT TRICHOME 15 [hp_X]/1 g; SOLANUM DULCAMARA TOP 15 [hp_X]/1 g; GRAPHITE 15 [hp_X]/1 g; GRINDELIA HIRSUTULA FLOWERING TOP 15 [hp_X]/1 g; HYPERICUM PERFORATUM 15 [hp_X]/1 g; IRIS VERSICOLOR ROOT 15 [hp_X]/1 g; LYCOPODIUM CLAVATUM SPORE 15 [hp_X]/1 g; DAPHNE MEZEREUM BARK 15 [hp_X]/1 g; RANUNCULUS BULBOSUS 15 [hp_X]/1 g; TOXICODENDRON PUBESCENS LEAF 15 [hp_X]/1 g; DELPHINIUM STAPHISAGRIA SEED 15 [hp_X]/1 g; SULFUR 15 [hp_X]/1 g; ECHINACEA, UNSPECIFIED 6 [hp_X]/1 g; THUJA OCCIDENTALIS LEAFY TWIG 15 [hp_X]/1 g; ZINC 15 [hp_X]/1 g; APIS MELLIFERA 15 [hp_X]/1 g; ARSENIC TRIOXIDE 15 [hp_X]/1 g
INACTIVE INGREDIENTS: SUCROSE

Shing-V 2587P

INDICATIONS & USAGE SECTION

Formulated for syptoms such as pain, burning, itching, swelling and skin eruptions.

OTC - ACTIVE INGREDIENT SECTION

Equal parts of Chamomilla 6x, Echinacea 6x, Apis mel. 15x, Arsenicum alb. 15x, Asterias 15x, Cantharis 15x, Cistus canadensis 15x, Croton 15x, Dolichos pruriens 15x, Dulcamara 15x, Graphites 15x, Grindelia 15x, Hypericum 15x, Iris vers. 15x, Lycopodium 15x, Mezereum 15x, Ranunculus bulb. 15x, Rhus tox 15x, Staphysag. 15x, Sulphur 15x, Thuja occ. 15x, Zinc. met. 15x.

OTC - PURPOSE SECTION

Formulated for symptoms such as pain, burning, itching, swelling and skin eruptions.

INACTIVE INGREDIENT SECTION

Gluten-free, non-GMO, organic beet-derived sucrose (lactose-free) pellets.

QUESTIONS SECTION

newtonlabs.net – Questions? 800.448.7256

Newton Laboratories, Inc. FDA Est # 1051203 - Conyers, GA 30013

WARNINGS SECTION

WARNINGS: Keep out of reach of children. Do not use if tamper-evident seal is broken or missing. If symptoms worsen or persist for more than a few days, consult a doctor. If pregnant or breast-feeding, ask a doctor before use.

OTC - PREGNANCY OR BREAST FEEDING SECTION

If pregnant or breast-feeding, ask a doctor before use.

OTC - KEEP OUT OF REACH OF CHILDREN SECTION

Keep out of reach of children.

DOSAGE & ADMINISTRATION SECTION

Directions: Ages 12 and up, take 6 pellets by mouth (ages 0 to 11, give 3 pellets) as need or as directed by a health professional. Under age 2, crush/dissolve pellets in purified water. Sensitive person begin with 1 pellet and gradually increase to full dose.